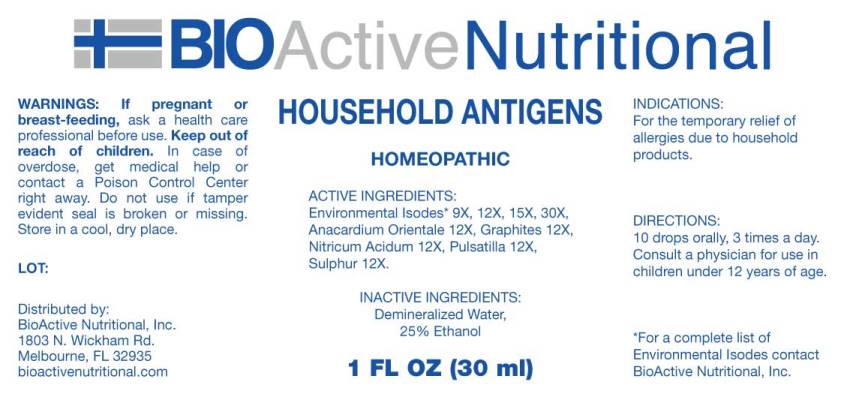 DRUG LABEL: Household Antigens
NDC: 43857-0537 | Form: LIQUID
Manufacturer: BioActive Nutritional
Category: homeopathic | Type: HUMAN OTC DRUG LABEL
Date: 20230714

ACTIVE INGREDIENTS: ACETONE 9 [hp_X]/1 mL; SODIUM TRIPOLYPHOSPHATE 9 [hp_X]/1 mL; PROPYLENE GLYCOL 9 [hp_X]/1 mL; BENZENE 9 [hp_X]/1 mL; AMMONIUM CHLORIDE 9 [hp_X]/1 mL; SODIUM LAURYL SULFATE 9 [hp_X]/1 mL; TURPENTINE OIL 9 [hp_X]/1 mL; SEMECARPUS ANACARDIUM JUICE 12 [hp_X]/1 mL; GRAPHITE 12 [hp_X]/1 mL; NITRIC ACID 12 [hp_X]/1 mL; PULSATILLA PRATENSIS WHOLE 12 [hp_X]/1 mL; SULFUR 12 [hp_X]/1 mL
INACTIVE INGREDIENTS: Water; ALCOHOL

DRUG FACTS:

ACTIVE INGREDIENTS:

Acetone 9X, 12X, 15X, 30X, Sodium Tripolyphosphate 9X, 12X, 15X, 30X, Propylene Glycol 9X, 12X, 15X, 30X, Benzinum 9X, 12X, 15X, 30X, Ammonium Muriaticum 9X, 12X, 15X, 30X, Sodium Lauryl Sulfate 9X, 12X, 15X, 30X, Terebinthina 9X, 12X, 15X, 30X, Anacardium Orientale 12X, Graphites 12X, Nitricum Acidum 12X, Pulsatilla (Pratensis) 12X, Sulphur 12X.

PURPOSE:

For the temporary relief of allergies due to household products.

WARNINGS:

If pregnant or breast-feeding, ask a health care professional before use.

Keep out of reach of children. In case of overdose, get medical help or contact a Poison Control Center right away.

Do not use if tamper evident seal is broken or missing.

Store in a cool, dry place.

KEEP OUT OF REACH OF CHILDREN.

In case of overdose, get medical help or contact a Poison Control Center right away.

DIRECTIONS:

10 drops orally, 3 times a day. Consult a physician for use in children under 12 years of age.

INDICATIONS:

For the temporary relief of allergies due to household products.

INACTIVE INGREDIENTS:

Demineralized Water, 25% Ethanol

QUESTIONS:

Distributed by:

BioActive Nutritional, Inc.

1803 N. Wickham Rd.

Melbourne, FL 32935

bioactivenutritional.com

*For a complete list of Environmental Isode Contact BioActive Nutritional, Inc.

PACKAGE DISPLAY LABEL:

BIOActive Nutritional

HOUSEHOLD ANTIGENS

HOMEOPATHIC

1 FL OZ (30 ml)